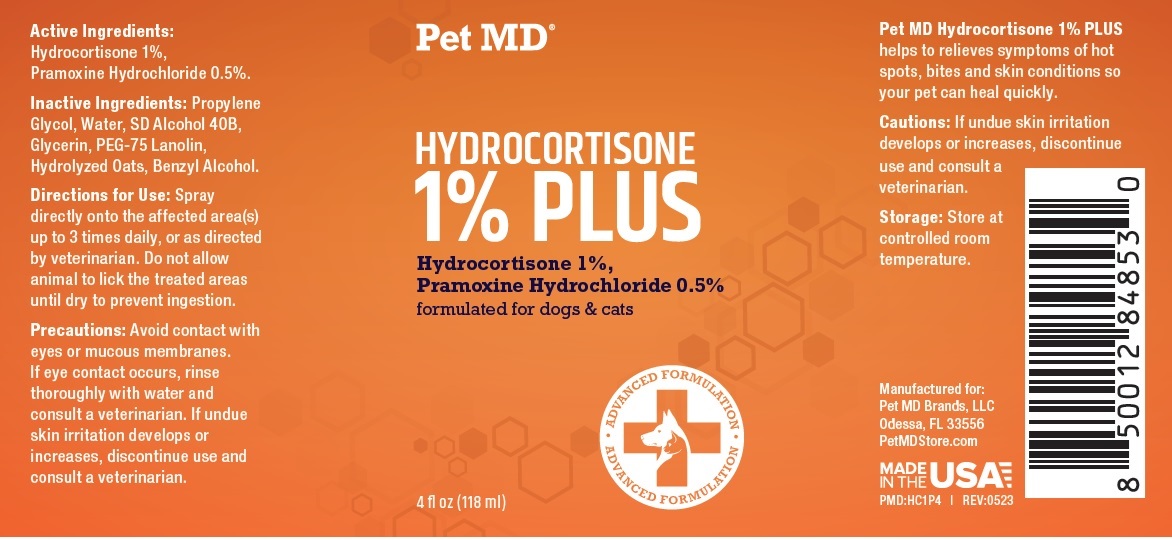 DRUG LABEL: Pet MD HYDROCORTISONE 1% PLUS
NDC: 86090-016 | Form: SPRAY
Manufacturer: Pet MD Brands, LLC
Category: animal | Type: OTC ANIMAL DRUG LABEL
Date: 20230831

ACTIVE INGREDIENTS: HYDROCORTISONE 1 g/100 mL; PRAMOXINE HYDROCHLORIDE 0.5 g/100 mL
INACTIVE INGREDIENTS: PROPYLENE GLYCOL; WATER; ALCOHOL; GLYCERIN; PEG-75 LANOLIN; OAT; BENZYL ALCOHOL

Pet MD® HYDROCORTISONE 1% PLUS

Active Ingredients:

Hydrocortisone 1%,
Pramoxine Hydrochloride 0.5%.

INDICATIONS AND USAGE

Pet MD Hydrocortisone 1% PLUS helps to relieve symptoms of hot spots, bites and skin conditions so your pet can heal quickly.

Inactive Ingredients:

Propylene Glycol, Water, SD Alcohol 40B, Glycerin, PEG-75 Lanolin, Hydrolyzed Oats, Benzyl Alcohol.

Directions for Use:

Spray directly onto the affected area(s) up to 3 times daily, or as directed by veterinarian. Do not allow animal to lick the treated areas until dry to prevent ingestion.

Precautions:

Avoid contact with eyes or mucous membranes. If eye contact occurs, rinse thoroughly with water and consult a veterinarian.

Cautions:

If undue skin irritation develops or increases, discontinue use and consult a veterinarian.

Storage:

Store at controlled room temperature.

formulated for dogs & cats

ADVANCED FORMULATION

Manufactured for:
Pet MD Brands, LLC
Odessa, FL 33556
PetMDStore.com

MADE IN THE USA